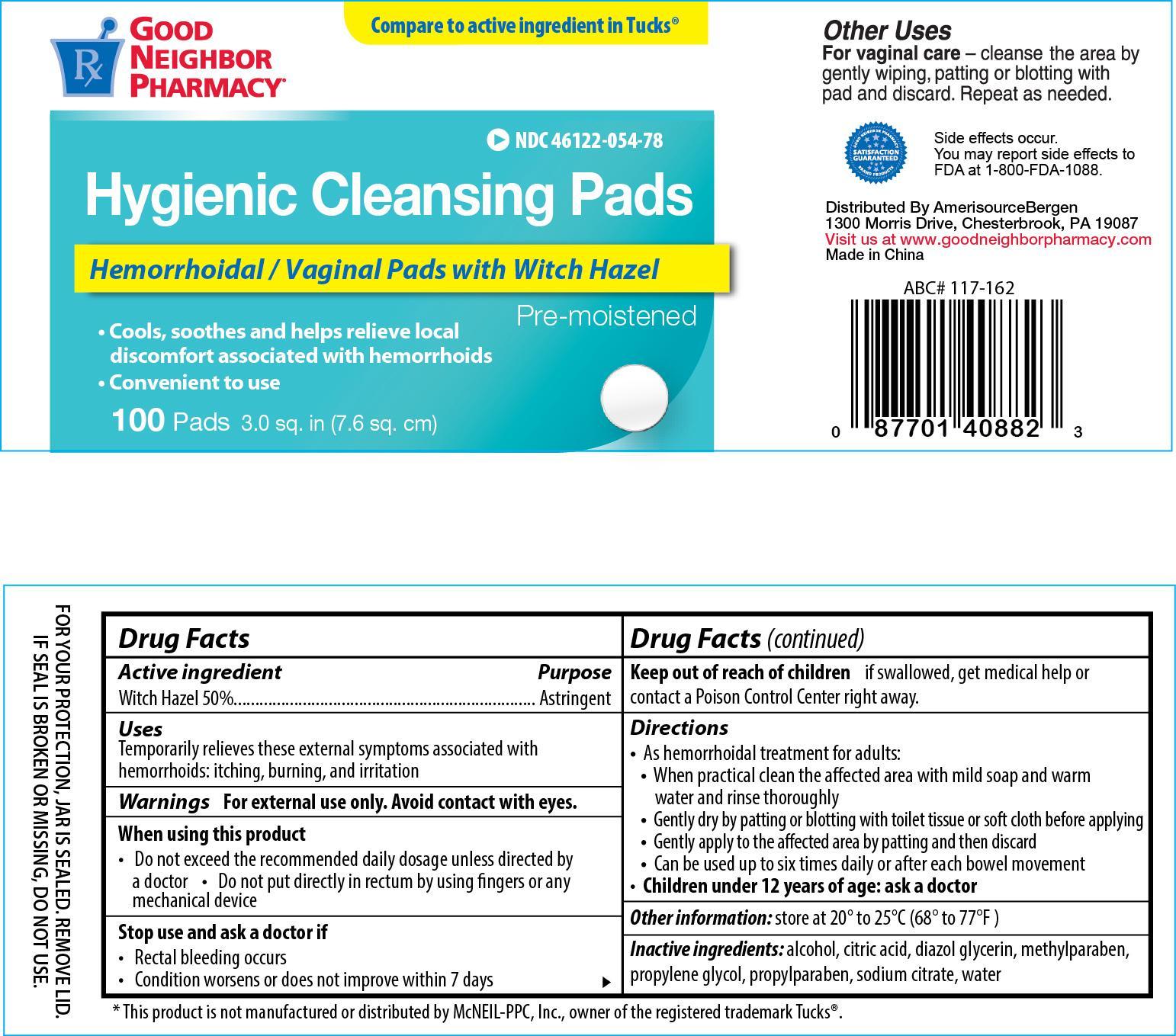 DRUG LABEL: GNP Hygienic Cleansing Pads
NDC: 46122-054 | Form: SOLUTION
Manufacturer: Amerisource Bergen
Category: otc | Type: HUMAN OTC DRUG LABEL
Date: 20130630

ACTIVE INGREDIENTS: WITCH HAZEL 0.5 mg/1 mg
INACTIVE INGREDIENTS: ALCOHOL; CITRIC ACID MONOHYDRATE; METHYLPARABEN; PROPYLENE GLYCOL; PROPYLPARABEN; SODIUM CITRATE; WATER

Drug Facts

Active ingredient Purpose

Witch Hazel 50%......................................................Astringent

PURPOSE

Uses Temporarily relieves these external symptoms associated with hemorrhoids: itching, burning, and irritation

WARNINGS

Warnings For external use only. Avoid contacts with eyes.

When using this product

- Do not exceed the recommended daily dosage unless directed by a doctor
- Do not put directly in rectum by using fingers or any mechanical device

Stop use and ask a doctor if

- Rectal bleeding occurs
- Condition worsens or does not improve within 7 days

Keep out of reach of children if swallowed, get medical help or contact a Poison Control Center right away.

Directions

- As hemorrhoidal treatment for adults:
- When practical clean the affected area with mild soap and warm water and rinse thoroughly
- Gently dry by patting or blotting with toilet tissue or soft cloth before applying
- Gently apply to the affected area by patting and then discard
- Can be used up to six times daily or after each bowel movement
- Children under 12 years of age: ask a doctor

Other information: store at 20° to 25°C (68° to 77°F)

INACTIVE INGREDIENT

Inactive ingredients: alcohol, citric acid, diazol glycerin, methylparaben, propylene glycol, propylparaben, sodium citrate, water

DOSAGE AND ADMINISTRATION

Distributed By:

Amerisource Bergen

1300 Morris Drive

Chesterbrook, PA 19087

Made in China